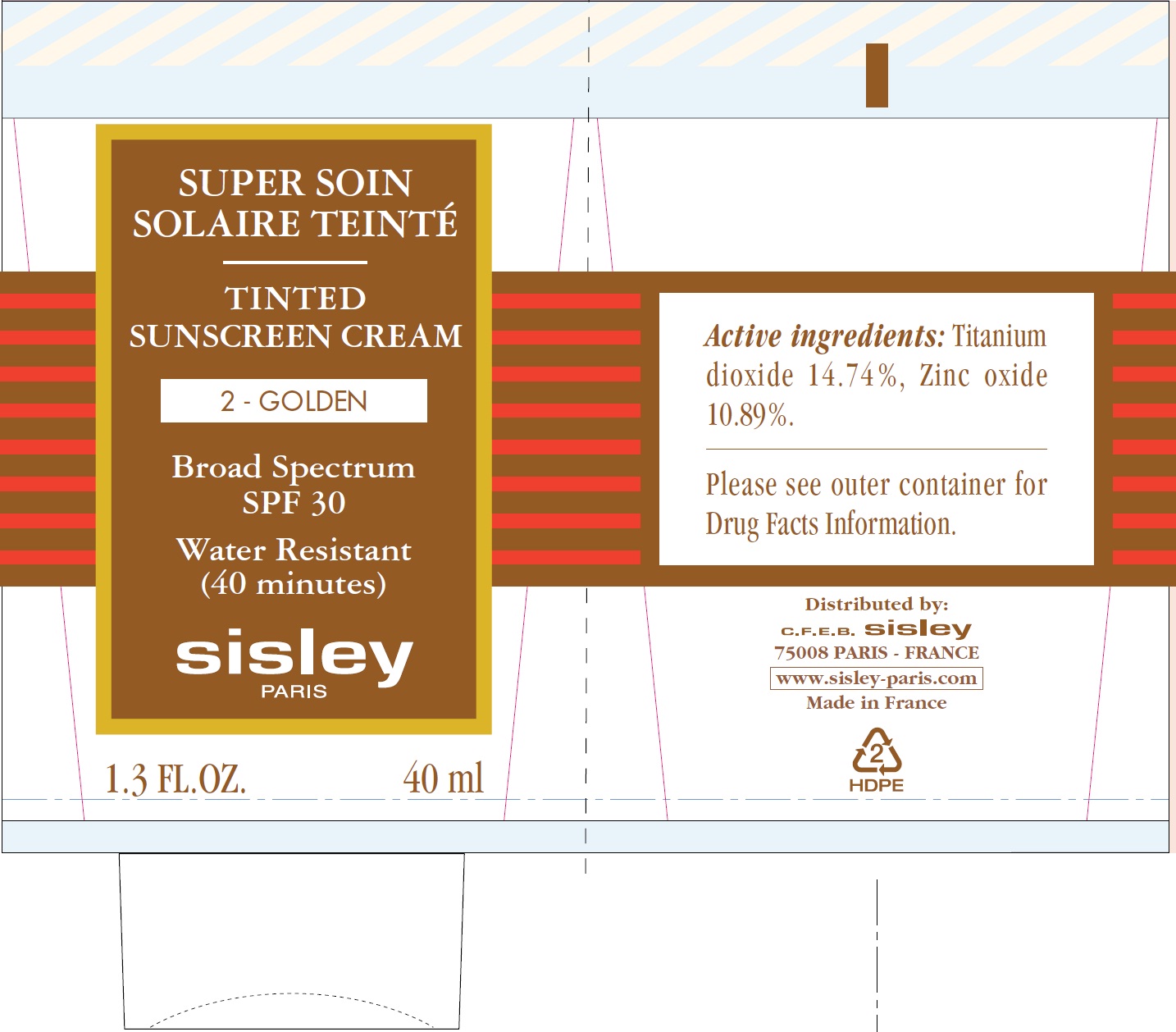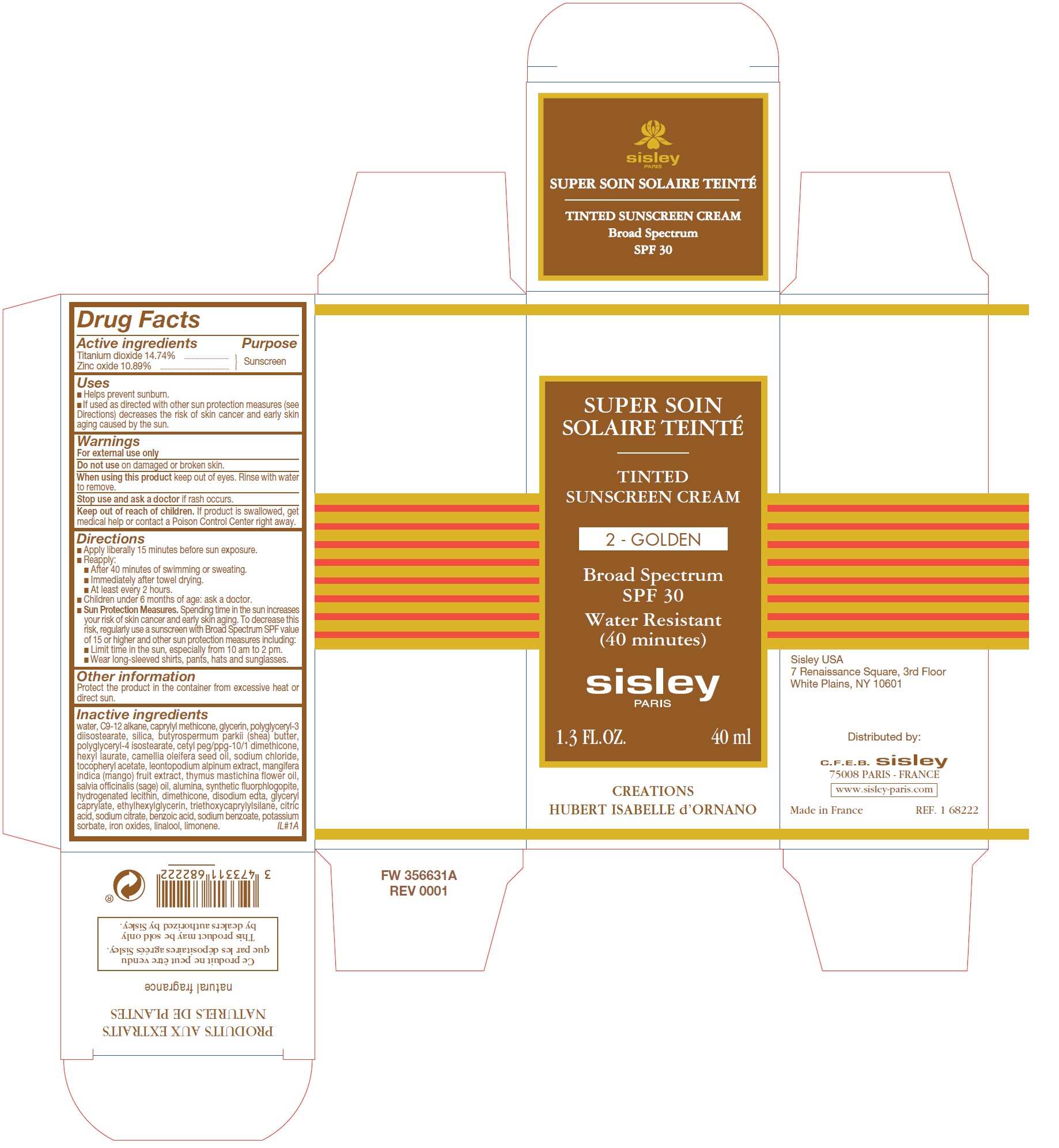 DRUG LABEL: Tinted Sunscreen SPF 30 2-Golden
NDC: 66097-008 | Form: CREAM
Manufacturer: C.F.E.B. - Sisley
Category: otc | Type: HUMAN OTC DRUG LABEL
Date: 20241210

ACTIVE INGREDIENTS: TITANIUM DIOXIDE 147.4 mg/1 mL; ZINC OXIDE 108.9 mg/1 mL
INACTIVE INGREDIENTS: WATER; CAPRYLYL TRISILOXANE; GLYCERIN; POLYGLYCERYL-3 DIISOSTEARATE; SILICON DIOXIDE; SHEA BUTTER; POLYGLYCERYL-4 ISOSTEARATE; HEXYL LAURATE; CAMELLIA OIL; SODIUM CHLORIDE; .ALPHA.-TOCOPHEROL ACETATE; THYMUS MASTICHINA FLOWERING TOP OIL; SAGE OIL; ALUMINUM OXIDE; DIMETHICONE; EDETATE DISODIUM; GLYCERYL CAPRYLATE; ETHYLHEXYLGLYCERIN; TRIETHOXYCAPRYLYLSILANE; CITRIC ACID MONOHYDRATE; SODIUM CITRATE; BENZOIC ACID; SODIUM BENZOATE; POTASSIUM SORBATE; FERRIC OXIDE RED; LINALOOL, (+/-)-

Tinted Sunscreen Cream SPF 30 2-Golden

Active ingredients

Titanium dioxide 14.74% Zinc oxide 10.89%

Purpose

Sunscreen

Uses

■ Helps prevent sunburn. ■ If used as directed with other sun protection measures (see Directions) decreases the risk of skin cancer and early skin aging caused by the sun.

Warnings

For external use only

Do not use

on damaged or broken skin.

When using this product

keep out of eyes. Rinse with water to remove.

Stop use and ask a doctor

if rash occurs.

Keep out of reach of children.

If product is swallowed, get medical help or contact a Poison Control Center right away.

Directions

■ Apply liberally 15 minutes before sun exposure. ■ Reapply: ■ After 40 minutes of swimming or sweating. ■ Immediately after towel drying. ■ At least every 2 hours. ■ Children under 6 months of age: ask a doctor. ■ Spending time in the sun increases your risk of skin cancer and early skin aging. To decrease this risk, regularly use a sunscreen with Broad Spectrum SPF value of 15 or higher and other sun protection measures including: ■ Limit time in the sun, especially from 10 am to 2 pm. ■ Wear long-sleeved shirts, pants, hats and sunglasses.
Sun Protection Measures.

Other information

Protect the product in the container from excessive heat or direct sun.

Inactive ingredients

water, C9-12 alkane, caprylyl methicone, glycerin, polyglyceryl-3 diisostearate, silica, butyrospermum parkii (shea) butter, polyglyceryl-4 isostearate, cetyl peg/ppg-10/1 dimethicone, hexyl laurate, camellia oleifera seed oil, sodium chloride, tocopheryl acetate, leontopodium alpinum extract, mangifera indica (mango) fruit extract, thymus mastichina flower oil, salvia officinalis (sage) oil, alumina, synthetic fluorphlogopite, hydrogenated lecithin, dimethicone, disodium edta, glyceryl caprylate, ethylhexylglycerin, triethoxycaprylylsilane, citric acid, sodium citrate, benzoic acid, sodium benzoate, potassium sorbate, iron oxides, linalool, limonene.